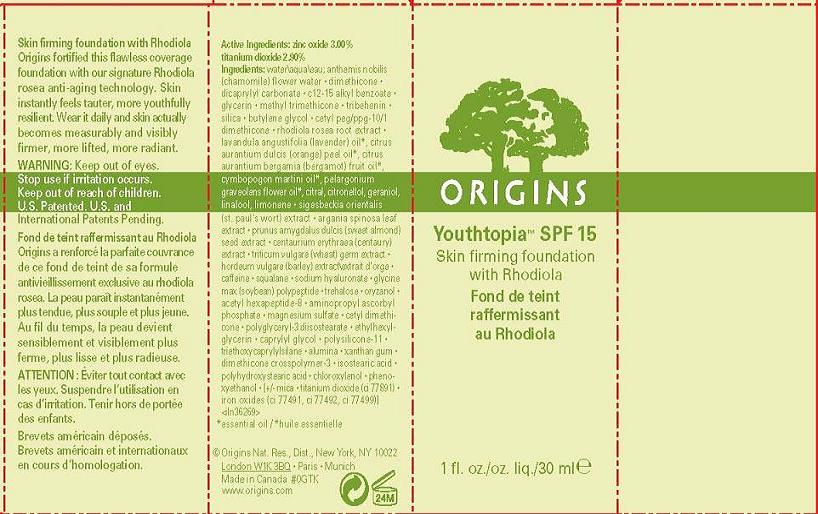 DRUG LABEL: YOUTHTOPIA SKIN FIRMING FOUNDATION
NDC: 59427-701 | Form: LIQUID
Manufacturer: ORIGINS NATURAL RESOURCES INC
Category: otc | Type: HUMAN OTC DRUG LABEL
Date: 20100730

ACTIVE INGREDIENTS: ZINC OXIDE 3.0 mL/100 mL; TITANIUM DIOXIDE 2.9 mL/100 mL

ACTIVE INGREDIENT

active ingredients: zinc oxide 3.00% [] titanium dioxide 2.90%

WARNINGS

warning: stop use if irritation occurs. keep out of reach of children

PACKAGE LABEL

principal display panel:

ORIGINS

YOUTHTOPIA SPF 15

SKIN FIRMING FOUNDATION WITH RHODIOLA

1 FL OZ/OZ LIQ/30 ML

ORIGINS NAT. RES. DISTR., NY, NY 10022